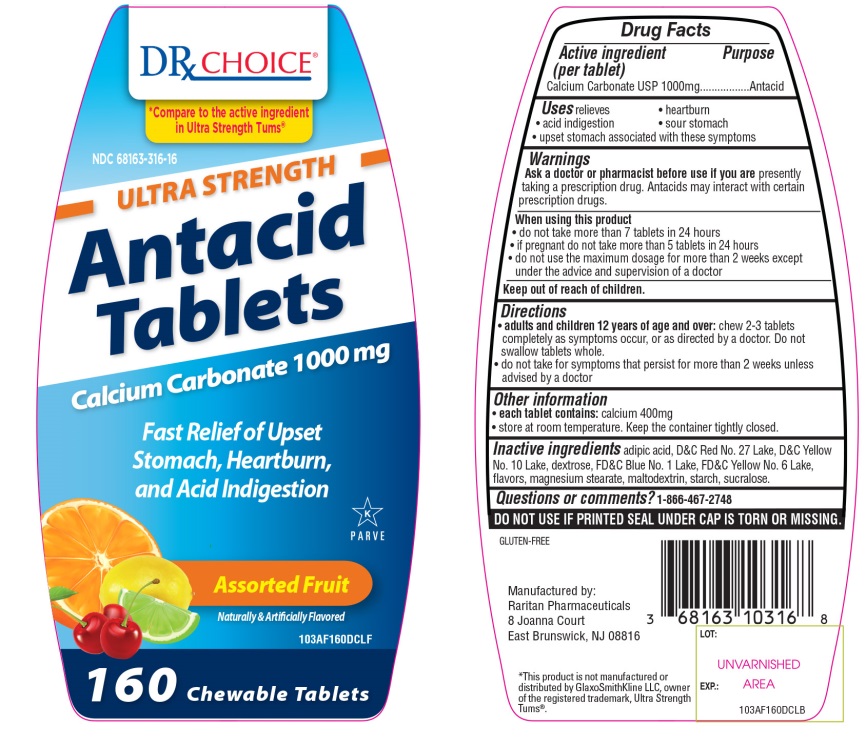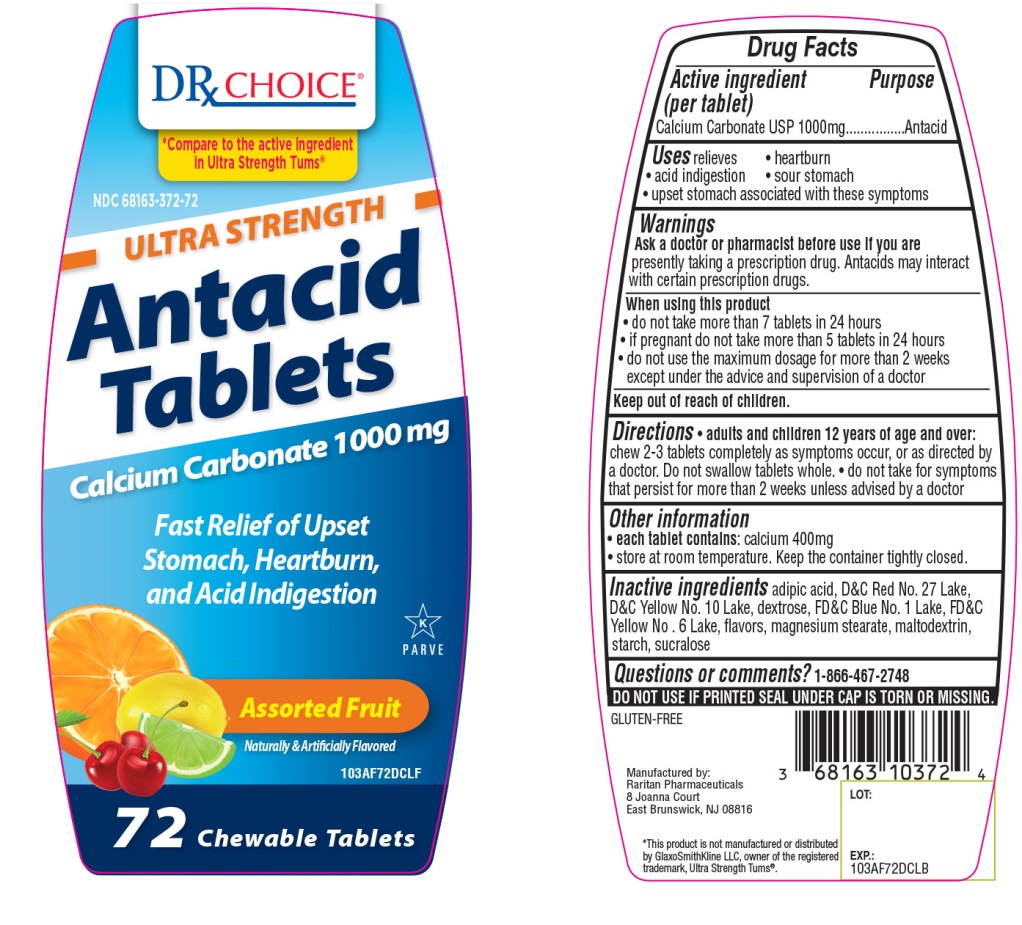 DRUG LABEL: Ultra Strength Antacid
NDC: 68163-316 | Form: TABLET, CHEWABLE
Manufacturer: Raritan Pharmaceuticals Inc
Category: otc | Type: HUMAN OTC DRUG LABEL
Date: 20210118

ACTIVE INGREDIENTS: CALCIUM CARBONATE 1000 mg/1 1
INACTIVE INGREDIENTS: ADIPIC ACID; D&C RED NO. 27; D&C YELLOW NO. 10; DEXTROSE, UNSPECIFIED FORM; FD&C BLUE NO. 1; FD&C YELLOW NO. 6; MAGNESIUM STEARATE; MALTODEXTRIN; STARCH, CORN; SUCRALOSE

DRx Choice Antacid Tablets 1000 Calcium Carbonate 1000 mg Ultra Strength Assorted fruits Flavor 160 Chewable Tablets

Active ingredient (per tablet)

Calcium Carbonate USP 1000 mg

Purpose

Antacid

Uses

relieves

• heartburn

• sour stomach

• acid indigestion

• upset stomach associated with these symptoms

Warnings

Ask a doctor or pharmacist before use if you are presentlytaking a prescription drug. Antacids may interact with certain prescription drugs.

When using this product

- do not take more than 7 tablets in 24 hours
- if pregnant do not take more than 5 tablets in 24 hours
- do not use the maximum dosage for more than 2 weeks except under the advice and supervision of a doctor.

Directions

- adults and children 12 years of age and over: chew 2-3 tablets completely as symptoms occur, or as directed by a doctor. Do not swallow tablets as whole.
- do not take for symptoms that persist for more than 2 weeks unless advised by a doctor

Other information

- each tablet contains: calcium 400 mg
- store at room temperature. Keep the container tightly closed

Inactive ingredients

adipic acid, D&C red No. 27 Lake, D&C yellow No. 10 Lake, dextrose, FD&C Blue No. 1 Lake, FD&C yellow No. 6 Lake, flavors, magnesium stearate, maltodextrin, , starch, sucralose.

Questions or comments?

1-866-467-2748

Safety sealed: Do not use if printed seal under cap is torn or missing

Package/Label Principal Display Panel

DRx CHOICE

Compare to the active ingredient in Ultra Strength TUMS®

ULTRA STRENGTH

Antacid Tablets

Calcium Carbonate 1000mg

Fast Relief of Upset stomach, Heartburn and Acid Indigestion

Assorted Fruit

Naturally &Artificially Flavored

GLUTEN-FREE

††This product is not manufactured or distributed by GlaxoSmithKline LLC, owner of the registered trademark, Ultra Strength Tums®

Manufactured by:

Raritan Pharmaceuticals

8 Joanna Court

East Brunswick, NJ 08816

Package label for 160 Chewable Tablets